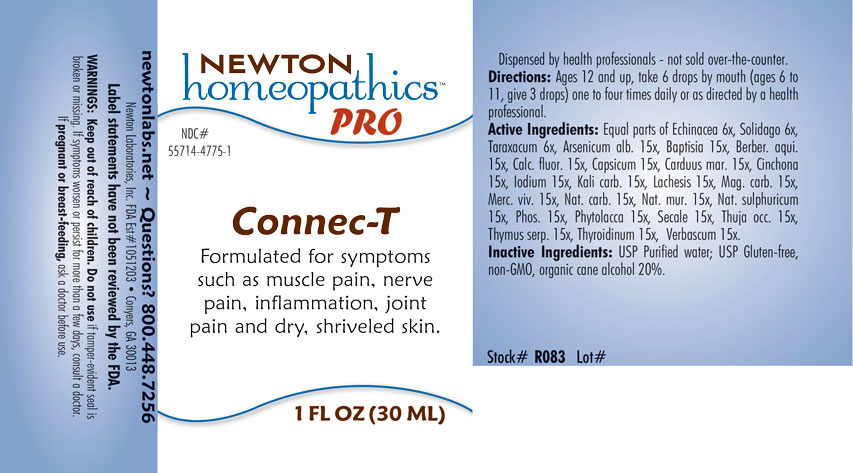 DRUG LABEL: Connec-T
NDC: 55714-4775 | Form: LIQUID
Manufacturer: Newton Laboratories, Inc.
Category: homeopathic | Type: HUMAN OTC DRUG LABEL
Date: 20201202

ACTIVE INGREDIENTS: ECHINACEA, UNSPECIFIED 6 [hp_X]/1 mL; VERBASCUM THAPSUS 15 [hp_X]/1 mL; CAPSICUM 15 [hp_X]/1 mL; SOLIDAGO VIRGAUREA FLOWERING TOP 6 [hp_X]/1 mL; PHOSPHORUS 15 [hp_X]/1 mL; PHYTOLACCA AMERICANA ROOT 15 [hp_X]/1 mL; THYMUS SERPYLLUM 15 [hp_X]/1 mL; THYROID, UNSPECIFIED 15 [hp_X]/1 mL; TARAXACUM OFFICINALE 6 [hp_X]/1 mL; CALCIUM FLUORIDE 15 [hp_X]/1 mL; MAGNESIUM CARBONATE 15 [hp_X]/1 mL; CLAVICEPS PURPUREA SCLEROTIUM 15 [hp_X]/1 mL; THUJA OCCIDENTALIS LEAFY TWIG 15 [hp_X]/1 mL; BAPTISIA TINCTORIA ROOT 15 [hp_X]/1 mL; CINCHONA OFFICINALIS BARK 15 [hp_X]/1 mL; IODINE 15 [hp_X]/1 mL; SODIUM SULFATE 15 [hp_X]/1 mL; SODIUM CHLORIDE 15 [hp_X]/1 mL; ARSENIC TRIOXIDE 15 [hp_X]/1 mL; SODIUM CARBONATE 15 [hp_X]/1 mL; LACHESIS MUTA VENOM 15 [hp_X]/1 mL; MERCURY 15 [hp_X]/1 mL; POTASSIUM CARBONATE 15 [hp_X]/1 mL; BERBERIS AQUIFOLIUM ROOT BARK 15 [hp_X]/1 mL; MILK THISTLE 15 [hp_X]/1 mL
INACTIVE INGREDIENTS: ALCOHOL; WATER

Connec-T 4775L

INDICATIONS & USAGE SECTION

Formulated for symptoms such as muscle pain, nerve pain, inflammation, joint pain and dry, shriveled skin.

DOSAGE & ADMINISTRATION

Directions: Ages 12 and up, take 6 drops by mouth (ages 6 to 11, give 3 drops) one to four times daily or as directed by a health professional.

OTC - ACTIVE INGREDIENT SECTION

Equal parts of Echinacea 6x, Solidago 6x, Taraxacum 6x, Arsenicum alb. 15x, Baptisia 15x, Berber. aqui. 15x, Calc. fluor. 15x, Capsicum 15x, Carduus mar. 15x, Cinchona 15x, Iodium 15x, Kali carb. 15x, Lachesis 15x, Mag. carb. 15x, Merc. viv. 15x, Nat. carb. 15x, Nat. mur. 15x, Nat. sulphuricum 15x, Phos. 15x, Phytolacca 15x, Secale 15x, Thuja occ. 15x, Thymus serp. 15x, Thyroidinum 15x, Verbascum 15x.

OTC - PURPOSE SECTION

Formulated for symptoms such as muscle pain, nerve pain, inflammation, joint pain and dry, shriveled skin.

INACTIVE INGREDIENT SECTION

Inactive Ingredients: USP Purified water; USP Gluten-free, non-GMO, organic cane alcohol 20%.

QUESTIONS SECTION

newtonlabs.net - Questions? 800.448.7256

Newton Laboratories, Inc. FDA Est # 1051203 Conyers, GA 30013

WARNINGS SECTION

WARNINGS: Keep out of reach of children. Do not use if tamper-evident seal is broken or missing. If symptoms worsen or persist for more than a few days, consult a doctor. If pregnant or breast-feeding, ask a doctor before use.

OTC - PREGNANCY OR BREAST FEEDING SECTION

If pregnant or breast-feeding, ask a doctor before use.

OTC - KEEP OUT OF REACH OF CHILDREN

Keep out of reach of children.